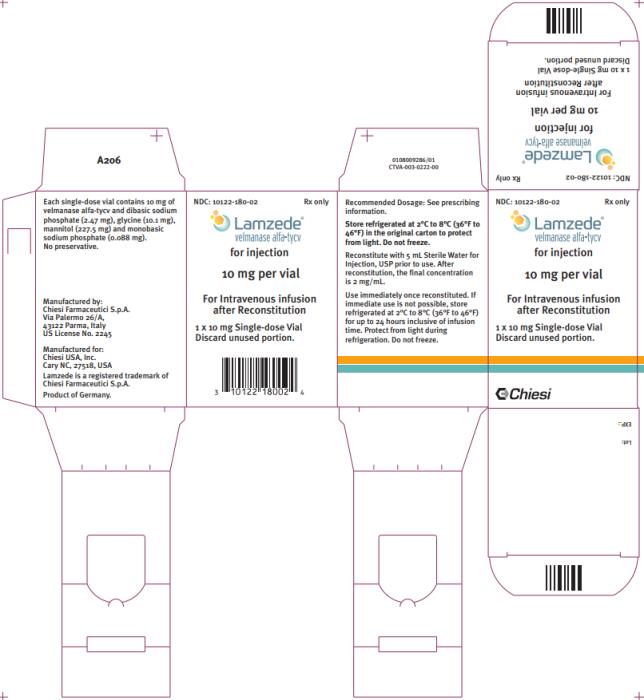 DRUG LABEL: Lamzede
NDC: 10122-180 | Form: INJECTION, POWDER, LYOPHILIZED, FOR SOLUTION
Manufacturer: Chiesi USA, Inc.
Category: prescription | Type: HUMAN PRESCRIPTION DRUG LABEL
Date: 20230221

ACTIVE INGREDIENTS: VELMANASE ALFA-TYCV 10 mg/1 1
INACTIVE INGREDIENTS: SODIUM PHOSPHATE, DIBASIC, UNSPECIFIED FORM 2.47 mg/1 1; GLYCINE 10.1 mg/1 1; MANNITOL 227.5 mg/1 1; SODIUM PHOSPHATE, MONOBASIC 0.088 mg/1 1

HIGHLIGHTS OF PRESCRIBING INFORMATION

These highlights do not include all the information needed to use LAMZEDE® safely and effectively. See full prescribing information for LAMZEDE.
LAMZEDE (velmanase alfa-tycv) for injection, for intravenous use
Initial U.S. Approval: 2023

WARNING: SEVERE HYPERSENSITIVITY REACTIONS

See full prescribing information for complete boxed warning.

Hypersensitivity Reactions Including Anaphylaxis

- Appropriate medical support measures, including cardiopulmonary resuscitation equipment, should be readily available. If a severe hypersensitivity reaction occurs, discontinue LAMZEDE immediately and initiate appropriate medical treatment. (5.1)

1 INDICATIONS AND USAGE

LAMZEDE is recombinant human lysosomal alpha-mannosidase indicated for the treatment of non-central nervous system manifestations of alpha-mannosidosis in adult and pediatric patients. (1)

2 DOSAGE AND ADMINISTRATION

- For females of reproductive potential, verify that the patient is not pregnant prior to initiating treatment. (2.1)
- Consider pretreating with antihistamines, antipyretics, and/or corticosteroids prior to LAMZEDE administration. (2.2)
- Recommended LAMZEDE dosage is 1 mg/kg (actual body weight) administered once every week as an intravenous infusion. (2.2)
- See the full prescribing information for dosage modifications due to hypersensitivity reactions or IARs. (2.3)
- See the full prescribing information for reconstitution and administration instructions. (2.4, 2.5)

3 DOSAGE FORMS AND STRENGTHS

For injection: 10 mg of velmanase alfa-tycv as a lyophilized powder in a single-dose vial for reconstitution. (3)

4 CONTRAINDICATIONS

None. (4)

5 WARNINGS AND PRECAUTIONS

- Infusion-Associated Reactions (IARs): If severe IARs occur, discontinue LAMZEDE and initiate appropriate medical treatment. (5.2)
- Embryo-Fetal Toxicity: May cause fetal harm. Advise females of reproductive potential to use effective contraception during treatment and for 14 days after the last dose if LAMZEDE is discontinued. (5.3, 8.1, 8.3)

6 ADVERSE REACTIONS

Most common adverse reactions (incidence > 20%) are hypersensitivity reactions including anaphylaxis (5.1), nasopharyngitis, pyrexia, headache, and arthralgia. (6.1)

To report SUSPECTED ADVERSE REACTIONS, contact Chiesi USA, Inc. at 1-888-661-9260 or FDA at 1-800-FDA-1088 or www.fda.gov/medwatch.

FULL PRESCRIBING INFORMATION

WARNING: SEVERE HYPERSENSITIVITY REACTIONS

Hypersensitivity Reactions Including Anaphylaxis

Patients treated with LAMZEDE have experienced hypersensitivity reactions, including anaphylaxis. Appropriate medical support measures, including cardiopulmonary resuscitation equipment, should be readily available during LAMZEDE administration. If a severe hypersensitivity reaction (e.g., anaphylaxis) occurs, discontinue LAMZEDE immediately and initiate appropriate medical treatment. In patients with severe hypersensitivity reaction, a desensitization procedure to LAMZEDE may be considered [see Warnings and Precautions (5.1)].

1 INDICATIONS AND USAGE

LAMZEDE is indicated for the treatment of non-central nervous system manifestations of alpha-mannosidosis in adult and pediatric patients.

2 DOSAGE AND ADMINISTRATION

2.1 Important Recommendations Prior to LAMZEDE Treatment Initiation

For females of reproductive potential, verify that the patient is not pregnant [see Use in Specific Populations (8.1, 8.3)].

2.2 Recommended Dosage and Administration

Prior to LAMZEDE administration, consider pre-treating with antihistamines, antipyretics, and/or corticosteroids [see Warnings and Precautions (5.1, 5.2)].

The recommended dosage of LAMZEDE is 1 mg/kg (actual body weight) administered once every week as an intravenous infusion.

The total volume of infusion is determined by the patient’s actual body weight and should be administered over a minimum of 60 minutes for patients weighing up to 49 kg. Patients weighing 50 kg and greater should be infused at a maximum infusion rate of 25 mL/hour to control the protein load [see Dosage and Administration (2.4)].

If one or more doses are missed, restart the treatment as soon as possible, as long as it is at least 3 days from the next scheduled dose. If it is within 3 days from the next scheduled dose, give only the next dose per schedule.

2.3 Dosage and Administration Modifications Due to Hypersensitivity Reactions and/or Infusion-Associated Reactions

In the event of a severe hypersensitivity reaction (including anaphylaxis) or severe infusion-associated reaction (IAR), immediately discontinue LAMZEDE administration and initiate appropriate medical treatment. For additional recommendations in the event of a severe hypersensitivity reaction or IAR, see Warnings and Precautions (5.1, 5.2).

In the event of a mild to moderate hypersensitivity reaction or a mild to moderate IAR, consider temporarily holding the infusion for 15 to 30 minutes, slowing the infusion rate to 25% to 50% of the recommended rate, and initiating appropriate medical treatment [see Warnings and Precautions (5.1, 5.2)].

If symptoms:

- Persist despite temporarily holding or slowing the infusion, stop the infusion and monitor the patient. If symptoms continue to persist, discontinue the infusion, and consider re-initiating the infusion within 7 to 14 days at 25% to 50% of the recommended rate with appropriate pretreatment.
- Subside following holding or slowing the infusion, resume infusion at 25% to 50% the recommended rate. If tolerated, increase the infusion rate by increments of 25% of the recommended rate until the recommended infusion rate is reached. Closely monitor the patient.

2.4 Reconstitution Instructions

Use aseptic technique during preparation. Reconstitute LAMZEDE in the following manner:

- Determine the number of LAMZEDE vials to be reconstituted based on the patient’s weight in kg and the recommended dose [see Dosage and Administration (2.2)]. Round the number of vials up to the next whole number.
- Remove vials from the refrigerator and set aside for approximately 30 minutes to allow vials to come to room temperature.
- Reconstitute each vial by slowly injecting 5 mL of Sterile Water for Injection, down the inside wall of each vial. Avoid adding the Sterile Water for Injection to the vial forcefully or directly onto the lyophilized powder to minimize foaming.
- Allow the reconstituted vials to stand on the table for 5 – 15 minutes. Then gently tilt and roll each vial for 15 – 20 seconds to enhance the dissolution process. Each vial will yield a concentration of 2 mg/mL. Do not invert, swirl, or shake the vials.
- Visually inspect the reconstituted solution in the vials for particulate matter and discoloration. The solution should be clear to slightly opalescent. Due to the nature of LAMZEDE, the solution may occasionally contain some proteinaceous particles in the form of thin white strands or translucent fibers which will be removed by the in line filter during infusion. Discard if opaque particles are present or the solution is discolored.
- Slowly withdraw the required volume from the vials with caution to avoid foaming in the syringe. If the volume of the solution exceeds one syringe capacity, prepare the required number of syringes in order to replace the syringe quickly during the infusion. Discard unused portion remaining in the vials.

Storage of the Reconstituted Solution

- If the reconstituted LAMZEDE vial is not used immediately, store the vial refrigerated at 2°C to 8°C (36°F to 46°F) for up to 24 hours inclusive of infusion time. Protect from light during refrigeration. Do not freeze.
- Reconstituted LAMZEDE vial must be infused within 10 hours after removal from the refrigerator, inclusive of total infusion time. Discard if not used within 10 hours.
- Infuse reconstituted solution within 24 hours from the time of preparation, which includes the storage time in the refrigerator, the time at room temperature, and the duration of the infusion.

2.5 Administration Instructions

- Use an infusion set equipped with a pump and a low protein binding, 0.2-micron, in-line filter to administer LAMZEDE. Do not shake the syringe.
- The total volume of infusion is determined by the patient’s actual body weight and should be administered over a minimum of 60 minutes for patients weighing up to 49 kg. Patients weighing 50 kg and greater should be infused at a maximum infusion rate of 25 mL/hour to control the protein load.
- When the last syringe is empty, replace the dosage syringe with a 20 mL syringe filled with 0.9% Sodium Chloride Injection, and then continue to infuse an additional 10 mL of 0.9% Sodium Chloride Injection through the infusion system to infuse the remaining fraction of LAMZEDE in the line to the patient.

3 DOSAGE FORMS AND STRENGTHS

For injection: 10 mg of velmanase alfa-tycv as a white to off-white lyophilized powder with a cake-like appearance in a single-dose vial for reconstitution.

4 CONTRAINDICATIONS

None.

5 WARNINGS AND PRECAUTIONS

5.1 Hypersensitivity Reactions Including Anaphylaxis

Hypersensitivity reactions including anaphylaxis have been reported in LAMZEDE-treated patients. In clinical trials, 19 (50%) LAMZEDE-treated patients (5 adult patients and 14 pediatric patients) experienced hypersensitivity reactions, including 2 (5%) patients (1 adult patient and 1 pediatric patient) who experienced anaphylaxis and an additional 3 (8%) pediatric patients who experienced severe hypersensitivity reactions that required medical treatment [see Clinical Studies (14)].

In the 5 patients who experienced anaphylaxis or severe hypersensitivity requiring medical treatment, 4 (80%) were anti-drug antibody (ADA) positive [see Clinical Pharmacology (12.6)].

Anaphylaxis and severe hypersensitivity signs and symptoms included cyanosis, hypotension, emesis, urticaria, erythema, facial swelling, pyrexia, and tremor.

Prior to LAMZEDE administration, consider pretreating with antihistamines, antipyretics, and/or corticosteroids. Appropriate medical support measures, including cardiopulmonary resuscitation equipment, should be readily available during LAMZEDE administration.

- If a severe hypersensitivity reaction (e.g., anaphylaxis) occurs, discontinue LAMZEDE immediately and initiate appropriate medical treatment. Consider the risks and benefits of re-administering LAMZEDE following severe hypersensitivity reactions (including anaphylaxis). Patients may be rechallenged using slower infusion rates. In patients with severe hypersensitivity reaction, desensitization measures to LAMZEDE may be considered. If the decision is made to readminister LAMZEDE, ensure the patient tolerates the infusion. If the patient tolerates the infusion, the rate may be increased to reach the recommended dosage.
- If a mild or moderate hypersensitivity reaction occurs, consider slowing the infusion rate or temporarily withholding the dose [see Dosage and Administration (2.3)].

5.2 Infusion-Associated Reactions

Infusion-associated reactions (IARs) have been reported in LAMZEDE-treated patients. In clinical trials 19 (50%) LAMZEDE-treated patients (3 adult and 16 pediatric patients) experienced IARs. Of these 19 patients, 5 (13 % of all patients) required pretreatment in the clinical trials. One LAMZEDE-treated patient in clinical trials discontinued due to recurrent IARs.

The most frequent symptoms of IARs that occurred in >10% of the population were pyrexia, chills, erythema, vomiting, cough, urticaria, rash and conjunctivitis. Similar symptoms were observed in adult and pediatric populations.

Prior to LAMZEDE administration, consider pretreating with antihistamines, antipyretics, and/or corticosteroids to reduce the risk of infusion-associated reactions (IARs). However, IARs may still occur in patients after receiving pretreatment.

- If a severe IAR occurs, discontinue LAMZEDE immediately and initiate appropriate medical treatment. Consider the risks and benefits of readministering LAMZEDE following a severe IAR. Patients may be rechallenged using slower infusion rates. Once a patient tolerates the infusion, the infusion rate may be increased to reach the recommended infusion rate.
- If a mild or moderate IAR occurs, consider slowing the infusion rate or temporarily withholding the dose [see Dosage and Administration (2.3)].

5.3 Embryo-Fetal Toxicity

Based on findings from animal reproduction studies, LAMZEDE may cause embryo-fetal harm when administered to a pregnant female. Administration of velmanase alfa-tycv to pregnant rats during the period of organogenesis caused skeletal and visceral malformations. In rats and rabbits, skeletal and visceral malformations were observed at exposures that were approximately 7- and 2.5-fold, respectively, those observed in patients treated at the recommended dose of 1 mg/kg.

The decision to continue or discontinue LAMZEDE treatment during pregnancy should consider the female’s need for LAMZEDE, the potential drug-related risks to the fetus, and the potential adverse outcomes from untreated maternal disease.

For females of reproductive potential, verify that the patient is not pregnant prior to initiating treatment with LAMZEDE. Advise females of reproductive potential to use effective contraception during treatment with LAMZEDE and for 14 days after the last dose if LAMZEDE is discontinued [see Use in Specific Populations (8.1, 8.3)].

6 ADVERSE REACTIONS

The following clinically significant adverse reactions are described elsewhere in the labeling:

- Hypersensitivity Reactions Including Anaphylaxis [see Warnings and Precautions (5.1)]
- Infusion-Associated Reactions (IARs) [see Warnings and Precautions (5.2)]

6.1 Clinical Trials Experience

Because clinical trials are conducted under widely varying conditions, adverse reaction rates observed in the clinical trials of a drug cannot be directly compared to rates in the clinical trials of another drug and may not reflect the rates observed in practice.

Adverse Reactions From Trial 1

The safety of LAMZEDE was evaluated in Trial 1, which included a total of 15 LAMZEDE-treated patients (8 adult patients aged 18-35 years old and 7 pediatric patients aged 6-17 years old; 9 male, 6 female) with alpha-mannosidosis [see Clinical Studies (14)]. All patients received LAMZEDE 1 mg/kg weekly via intravenous infusion for 52 weeks.

A serious adverse reaction of acute renal failure was reported in 1 (7%) LAMZEDE-treated patient (see Description of Selected Adverse Reactions).

Table 1 lists adverse reactions that occurred in at least 2 LAMZEDE-treated patients in Trial 1.

Table 1: Adverse Reactions (≥2 patients) in Adult and Pediatric Patients with Alpha-Mannosidosis Treated with LAMZEDE in Trial 1
Adverse Reaction | LAMZEDE N=15 n (%) | Placebo N=10 n (%)
Nasopharyngitis | 10 (66) | 7 (70)
Pyrexia | 6 (40) | 5 (50)
Headache | 5 (33) | 3 (30)
Arthralgia | 3 (20) | 1 (10)
Acute tonsillitis | 2 (13) | 0
Urinary tract infection^1 | 2 (13) | 1 (10)
Eye pruritus | 2 (13) | 0
Gastroenteritis | 2 (13) | 0
Hypersensitivity | 2 (13) | 0
Influenza | 2 (13) | 0
Syncope | 2 (13) | 0
Toothache | 2 (13) | 0
Back pain | 2 (13) | 1 (10)
Ear infection | 2 (13) | 1 (10)

^1 “Urinary tract infection” is composed of similar terms.

Adverse Reactions from Trials 2 and 3

In Trial 2, 5 pediatric patients aged 3 to 5 years old (3 male, 2 female) with alpha-mannosidosis received LAMZEDE weekly for a mean exposure of 121 weeks [see Clinical Studies (14)]. One patient treated with LAMZEDE (20%) presented serious reactions (chills and hyperthermia on the same occasion). The adverse reactions that occurred in at least 2 of 5 patients (and are in addition to the adverse reactions already identified in Trial 1 above) included: cough, otitis media, rhinitis, conjunctivitis, fall, ligament sprain, oropharyngeal pain, swelling face, and upper respiratory tract infection.

Trial 3 is an integrated analysis that pooled the cumulative databases from LAMZEDE phase 1, 2, and 3 trials in patients with alpha-mannosodosis. A total of 33 patients (20 male, 13 female) aged 6 to 35 years old (14 adults, 19 pediatric) received LAMZEDE weekly for a mean exposure of 89 weeks in adult patients and 155 weeks in pediatric patients.

One patient was withdrawn from the trial due to repeated IARs and successfully reintroduced after 89 weeks of pause.

The adverse reactions that occurred in at least 10% of patients (and are in addition to the adverse reactions already identified in Trial 1 and 2 above) included abdominal pain upper, contusion, excoriation, post-lumbar puncture syndrome, wound, weight increased, erythema, rash, and tooth extraction.

Description of Selected Adverse Reactions

Acute Renal Failure

One patient out of 38 (3%) experienced one episode of acute renal failure. This patient paused LAMZEDE treatment for 4 weeks and acute renal failure resolved within 12 weeks of diagnosis. This patient is noted to have received the concomitant medication of ibuprofen.

Immunoglobulin A Vasculitis

One episode of immunoglobulin A vasculitis (IgAV), reported as Henoch Schonlein Purpura, occurred in one patient out of 38 (3%) who developed high anti-drug antibody (ADA) levels.

Seizure

One patient out of 38 (3%), with no prior history of seizures experienced more than one episode of seizures. A relationship between the occurrence of seizures in this patient and exposure to LAMZEDE cannot be excluded.

Pediatric Patients

Hypersensitivity reactions overall were reported in 36% of adult patients and 58% of pediatric patients.

Immunogenicity: Anti-Drug Antibody-Associated Adverse Reactions

Infusion-associated reactions (including anaphylaxis and severe hypersensitivity reactions) occurred in a higher incidence in LAMZEDE-treated patients who developed anti-velmanase alfa-tycv antibodies (anti-drug antibodies, ADA) compared to patients who were ADA-negative (80% versus 20%) [see Clinical Pharmacology (12.6)].

In Trial 1 following treatment with LAMZEDE for up to 52 weeks, 1 out of 5 ADA-positive patients developed severe hypersensitivity and this patient developed the highest ADA level among all the ADA-positive patients in the trial. In Trial 2 following treatment with LAMZEDE for up to 174 weeks, 2 out of 4 ADA-positive pediatric patients experienced IARs. In Trial 3, 3 out of 33 patients (9.1%) reported IARs; two of these patients were ADA positive (one of these two patients is described in Trial 1); one patient was ADA negative.

6.2 Postmarketing Experience

The following adverse reactions have been identified during postapproval use of velmanase alfa outside of the United States. Because these reactions are reported voluntarily from a population of uncertain size, it is not always possible to reliably estimate their frequency or establish a causal relationship to drug exposure.

Cardiac disorders: aortic valve incompetence, palpitations, tachycardia

Ear and labyrinth disorders: deafness

Eye disorders: lacrimation increased

Gastrointestinal disorders: odynophagia

General disorders and administration site conditions: asthenia, fatigue

Infections and infestations: endocarditis, staphylococcal infection, bacterial disease carrier, furuncle

Metabolism and nutrition disorders: decreased appetite

Musculoskeletal and connective tissue disorders: joint swelling, joint warmth

Nervous system disorders: ataxia, nervous system disorder, somnolence

Psychiatric disorders: psychotic disorder, agitation, encopresis, nervousness

Respiratory, thoracic and mediastinal disorders: pharyngeal edema, wheezing

Skin, subcutaneous tissue disorders: angioedema

Vascular disorders: vascular fragility, hypotension

8 USE IN SPECIFIC POPULATIONS

8.1 Pregnancy

Risk Summary

Based on findings from animal reproduction studies, LAMZEDE may cause embryo-fetal harm when administered to a pregnant female. In animal reproduction studies, major visceral malformations were observed in rats and rabbits when velmanase alfa-tycv was administered in pregnant rats and rabbits during the period of organogenesis. These malformations were observed in rats at the highest dose level, at exposures that were approximately 7-fold the recommended dose in patients of 1 mg/kg. Malformations occurred at all dose levels in rabbits with the highest dose exposures approximately 2.5-fold the recommended patient dose of 1 mg/kg (see Data).

There are no available data on LAMZEDE use in pregnant females to evaluate a drug-associated risk of major birth defects, miscarriage or other adverse maternal or fetal outcomes. Advise the pregnant female of the potential risk to the fetus. The decision to continue or discontinue LAMZEDE treatment during pregnancy should consider the female’s need for LAMZEDE, the potential drug-related risks to the fetus, and the potential adverse outcomes from untreated maternal disease.

The background risk of major birth defects and miscarriage for the indicated population is unknown. All pregnancies have a background risk of birth defects, loss, or other adverse outcomes. In the U.S. general population, the estimated background risk of major birth defects and miscarriage in clinically recognized pregnancies is 2 to 4% and 15 to 20%, respectively.

Data

Animal Data

In an embryo-fetal development study in the rat, velmanase alfa-tycv was administered during the period of organogenesis from gestation day (GD) 6 to GD 17. Major malformations and variations were observed at exposures that were approximately 7-fold greater than the recommended dose of 1 mg/kg. Treatment-related major malformations included cleft palate, cleft palatine skull, severely bent pelvic girdle, and duplicated sternebrae.

In an embryofetal development study in the rabbit, administration of velmanase alfa-tycv from GDs 6 through 18 was associated with skeletal and/or visceral malformations, which occurred at exposures that were approximately 2.5-fold greater than those observed in patients treated at the 1 mg/kg dose level. Major malformations observed in rabbits included incomplete intraventricular septum; severely reduced size of one or more lung lobe; unilateral renal agenesis; unilateral ureter; diaphraghmatic hernia involving one or more lobe of the liver; hydrocephaly; single olfactory lobe; cystic dilatation of the cerebellum; malformed cervical, thoracic, caudal, and/or sacral vertebrae; and fused, absent, or vestigial ribs.

In the pre- and post-natal development study in rats, velmanase alfa-tycv was administered intravenously every 3 days at 0, 3.3, 10, and 30 mg/kg from GD 6 to lactation day 20. Velmanase alfa-tycv did not induce effects on maternal reproductive function or on developmental and reproductive parameters of male and female offspring; thus, the maternal and developmental NOAELs were 30 mg/kg. Exposures at this dose, based on the embryo-fetal development study, were estimated to be approximately 10-fold greater than the 1 mg/kg dose of velmanase alfa-tycv.

8.2 Lactation

Risk Summary

There are no data on the presence of velmanase alfa-tycv or its metabolite in either human or animal milk, the effects on the breastfed infant, or the effects on milk production. The developmental and health benefits of breastfeeding should be considered along with the mother’s clinical need for LAMZEDE and any potential adverse effects on the breastfed infant from velmanase alfa-tycv or from the underlying maternal condition.

8.3 Females and Males of Reproductive Potential

LAMZEDE may cause embryo-fetal harm when administered to a pregnant female [see Use in Specific Populations (8.1)].

Pregnancy Testing

For females of reproductive potential, verify that the patient is not pregnant prior to initiating treatment with LAMZEDE.

Contraception

Females

Advise females of reproductive potential to use effective contraception during treatment and for 14 days after the last dose if LAMZEDE is discontinued.

8.4 Pediatric Use

The safety and effectiveness of LAMZEDE for the treatment of alpha-mannosidosis have been established in pediatric patients.

Use of LAMZEDE for this indication is supported by evidence from an adequate and well-controlled clinical trial in adult and pediatric patients, and from an open label trial in 5 pediatric patients (younger than 6 years of age) [see Clinical Studies (14)].

LAMZEDE-treated pediatric patients reported a higher incidence of hypersensitivity reactions compared to LAMZEDE-treated adult patients [see Warnings and Precautions (5.1), Adverse Reactions (6.1)].

8.5 Geriatric Use

Alpha-mannosidosis is largely a disease of pediatric and young adult patients. Clinical trials of LAMZEDE did not include patients 65 years of age and older.

11 DESCRIPTION

Velmanase alfa-tycv, is lysosomal alpha-mannosidase produced by recombinant DNA technology in Chinese Hamster Ovary (CHO) cells. The amino acid sequence of the monomeric protein is identical to the naturally occurring human enzyme, alpha-mannosidase. Velmanase alfa-tycv has an approximate molecular weight of 130 kDa.

LAMZEDE (velmanase alfa-tycv) for injection is a sterile, preservative-free, white to off-white lyophilized powder with a cake-like appearance for intravenous infusion after reconstitution. Each single-dose vial contains 10 mg of velmanase alfa-tycv and the inactive ingredients dibasic sodium phosphate (2.47 mg), glycine (10.1 mg), mannitol (227.5 mg) and monobasic sodium phosphate (0.088 mg). After reconstitution with 5 mL Sterile Water for Injection, USP the resultant concentration is 2 mg/mL with pH of 7.5 ± 0.5.

12 CLINICAL PHARMACOLOGY

12.1 Mechanism of Action

Alpha-mannosidosis is a lysosomal storage disease that results from reduced activity of the enzyme alpha-mannosidase, caused by gene variants in Mannosidase Alpha Class 2B Member 1. Alpha-mannosidase catalyzes the degradation of accumulated mannose-containing oligosaccharides. The deficiency of alpha-mannosidase causes an intra-lysosomal accumulation of mannose-rich oligosaccharides in various tissues. Velmanase alfa-tycv provides an exogenous source of alpha-mannosidase. Velmanase alfa-tycv is internalized via binding to the mannose-6-phosphate receptor on the cell surface and transported into lysosomes where it is thought to exert enzyme activity.

12.2 Pharmacodynamics

Serum oligosaccharide concentrations are elevated in patients with alpha-mannosidosis. In clinical studies, serum oligosaccharide concentrations were quantified by assessment of 2-mannose oligosaccharides. LAMZEDE treatment resulted in reductions of serum oligosaccharide concentrations in patients with alpha-mannosidosis [see Clinical Studies (14)].

12.3 Pharmacokinetics

The pharmacokinetics of velmanase alfa-tycv were evaluated in adult patients with alpha-mannosidosis and are presented as mean (standard deviation, SD) unless otherwise specified. The steady state maximum plasma velmanase alfa-tycv concentration (Cmax) was 7.9 (0.9) μg/mL and area under the concentration-time curve (AUC0-t) was 159.8 (24.4) μg∙h/mL at the approved recommended dosage of 1 mg/kg.

Distribution

The volume of distribution of velmanase alfa-tycv was 276 (43) mL/kg in patients with alpha-mannosidosis.

Elimination

The total body clearance of velmanase alfa-tycv was 5.7 (0.9) mL/h/kg and the mean terminal half-life (t1/2) was 33.6 hours in patients with alpha-mannosidosis.

Metabolism

Velmanase alfa-tycv is expected to be metabolized into small peptides by catabolic pathways.

Specific Population

Pediatric Patients

In pediatric patients (6 to 17 years of age) with alpha-mannosidosis, the Cmax and AUC0-t at steady state were 6.6 (1.0) μg/mL and 109.8 (17.8) μg∙h/mL, respectively, at the recommended dose of 1 mg/kg velmanase alfa-tycv administered once a week.

In pediatric patients (3 to <6 years of age) with alpha-mannosidosis, the Cmax and AUC0-t at steady state were 7.0 (2.3) μg/mL and 75.9 (39.7) μg∙h/mL at the recommended dose of 1 mg/kg velmanase alfa-tycv amininistered once a week.

12.6 Immunogenicity

The observed incidence of anti-drug antibodies is highly dependent on the sensitivity and specificity of the assay. Differences in assay methods preclude meaningful comparisons of the incidence of anti-drug antibodies in the studies described below with the incidence of anti-drug antibodies in other studies, including those of velmanase alfa-tycv or of other velmanase alfa products.

In Trial 2 following 104 weeks treatment with LAMZEDE [see Clinical Studies (14)], 4 out of 5 pediatric patients (80%) developed anti-velmanase alfa-tycv antibodies (anti-drug antibodies, ADA). Three out of 4 ADA-positive patients (75%) developed neutralizing antibodies that inhibit velmanase alfa-tycv enzyme activity.

In Trial 3 [see Adverse Reactions (6.1)], 33 patients (10 adult, 23 pediatric) received LAMZEDE for up to 209 weeks. Among the 33 patients, 5 patients (1 adult and 4 pediatric) (15%) had ADA before treatment with LAMZEDE and for 1 patient the ADA level increased after treatment with LAMZEDE. Four other patients (1 adult and 3 pediatric) (12%) developed ADA after treatment with LAMZEDE. ADA positive samples were tested for neutralizing antibodies that inhibit velmanase alfa-tycv enzyme activity (NAb) during treatment in Trial 1. Four patients with ADA positive results also had positive NAb results during treatment with LAMZEDE. However, NAb positive results of similar magnitude were detected in 4 patients during treatment with placebo.

Neutralizing antibodies that inhibit cellular uptake of velmanase alfa-tycv have not been characterized.

Development of ADA was associated with lower plasma concentrations of velmanase alfa-tycv. Two pediatric patients who developed ADA had reduced pharmacodynamic responses in reduction of serum oligosaccharides at the time when high ADA levels were observed.

Infusion associated reactions (IARs) occurred in 2 patients in Trial 2 and 2 patients in Trial 3 who developed ADA compared to 2 patients in Trial 2 and 1 patient in Trial 3 who were ADA-negative [see Warnings and Precautions (5.1) and Adverse Reactions (6.1)].

13 NONCLINICAL TOXICOLOGY

13.1 Carcinogenesis, Mutagenesis, Impairment of Fertility

Carcinogenesis

Animal studies to evaluate the carcinogenic potential of velmanase alfa-tycv have not been conducted. In the pre- and postnatal development study in the rat, one female at the 30 mg/kg dose level developed a malignant histiocytic sarcoma of the ovary. A relationship to treatment for this tumor cannot be excluded. The AUC associated with tumor formation in this study was approximately 10-fold greater than those observed in patients treated at the 1 mg/kg dose level.

Mutagenesis

Studies to evaluate the mutagenic potential of velmanase alfa-tycv have not been conducted.

Impairment of Fertility

Intravenous administration of velmanase alfa-tycv twice-weekly for two weeks prior to pairing, through day 6 of gestation, showed no adverse effects on fertility parameters in rats. Based on data from the embryofetal study, exposures in the fertility study were approximately 10-fold greater than those observed in patients treated at the 1 mg/kg dose level.

14 CLINICAL STUDIES

Trial 1

Trial 1 (NCT01681953) was a phase 3 multicenter, randomized, double-blinded, placebo-controlled, parallel group trial in adult and pediatric patients with alpha-mannosidosis. The trial evaluated the efficacy of LAMZEDE over 52 weeks at a dose of 1 mg/kg given weekly as an intravenous infusion. A total of 25 patients were enrolled (14 males, 11 females), including 13 adult patients (age range: ≥18 to 35 years; mean: 25 years) and 12 pediatric patients (age range: ≥6 to <18 years; mean: 11 years); all patients were White. Ethnicity data were not collected. All patients had alpha-mannosidase activity below 11% of normal and in the range of 8 to 29 µmol/h/mg at baseline. All patients but one were naïve to LAMZEDE. Fifteen patients (8 adult and 7 pediatric) received LAMZEDE and 10 patients (5 adult and 5 pediatric) received placebo. All patients completed the trial.

The efficacy results for the clinical endpoints assessed at 12 months, 3-minute stair climbing test (3MSCT), 6-minute walking test (6MWT) and forced vital capacity (FVC) (% predicted), favored the LAMZEDE group and were supported by a reduction in serum oligosaccharide concentration. The results of 3MSCT, 6MWT, FVC (% predicted), and serum oligosaccaride concentrations are presented in Table 2.

Table 2: Change from Baseline in Clinical Endpoints and Serum Oligosaccharide in LAMZEDE- or Placebo-Treated Adult and Pediatric Patients with Alpha-Mannosidosis Over 12 Months
 | LAMZEDE (n=15) | Placebo (n=10) | Treatment difference (95% CI)
3MSCT (steps/min)
Baseline mean (SD) | 52.9 (11.2) | 55.5 (16.0) | --
Mean absolute change from baseline (SD) | 0.6 (8.6) | -2.4 (5.5) | 2.6 (-3.8, 9.1)
Mean relative change (%) from baseline (SD) | 0.5 (16.1) | -3.6 (13.1) | 3.4 (-9.5, 16.3)
FVC (% predicted)
Baseline mean (SD) | 81.7 (20.7) | 90.4 (10.4) | --
Mean absolute change from baseline (SD) | 8.2 (9.9) | 2.0 (12.6) | 5.5 (-5.0, 16.1)
Mean relative change (%) from baseline (SD) | 11.4 (13.1) | 1.9 (15.4) | 7.4 (-5.7, 20.5)
6MWT (meters)
Baseline mean (SD) | 459.6 (72.3) | 465.7 (140.5) | --
Mean absolute change from baseline (SD) | 4.4 (46.1) | -4.6 (40.8) | 7.4 (-30.7, 45.5)
Mean relative change (%) from baseline (SD) | 1.2 (9.8) | -0.8 (10.8) | 1.6 (-7.2, 10.4)
Serum oligosaccharides (μmol/L)
Baseline mean (SD) | 6.8 (1.2) | 6.6 (1.9) | --
Mean absolute change from baseline (SD) | -5.1 (1.2) | -1.6 (1.7) | -3.5 (-4.4, -2.6)
Mean relative change (%) from baseline (SD) | -75.8 (11.2) | -20.3 (24.0) | -55.6 (-69.3, -41.9)

Mean = sample mean and SD = standard deviation. For each endpoint, the treatment difference in the adjusted means (95% CI) were calculated using an analysis of covariance that included baseline age, baseline value of the endpoint as covariates. Missing data of FVC (% predicted) were not imputed.

Trial 2

LAMZEDE was investigated in a single arm trial in pediatric alpha-mannosidosis patients less than 6 years of age (NCT02998879). All patients had alpha-mannosidase activity below 10% of normal at baseline.The trial enrolled five patients ranging from 3.7 to 5.9 years of age, with a mean age of 4.5 years. Four patients were White, race was not recorded for 1 patient; and 3 were male and 2 were female. Patients received LAMZEDE 1 mg/kg as intravenous infusion once weekly (4 patients for 24 months, 1 patient for 40 months).

The mean (SD) absolute and percentage changes from Baseline for serum oligosaccharides at 24 months were -7.7 (4.27) μmol/L and -65.8% (23.1%) respectively.

16 HOW SUPPLIED/STORAGE AND HANDLING

How Supplied

LAMZEDE (velmanase alfa-tycv) for injection is supplied as a white to off-white lyophilized powder with a cake-like appearance in a single-dose vial. Each vial contains 10 mg of velmanase alfa-tycv. LAMZEDE is available as:

- One 10 mg single-dose vial in a carton: NDC 10122-180-02
- Five 10 mg single-dose vials in a carton: NDC 10122-180-05
- Ten 10 mg single-dose vials in a carton: NDC 10122-180-10

Storage and Handling

Store refrigerated at 2°C to 8°C (36°F to 46°F) in the original carton to protect from light. Do not freeze.

17 PATIENT COUNSELING INFORMATION

Hypersensitivity Reactions Including Anaphylaxis and Infusion-Associated Reactions (IARs)

Advise the patient and caregiver that reactions related to the infusion may occur during and after LAMZEDE treatment, including anaphylactic reactions, other serious or severe hypersensitivity reactions, and IARs. Inform the patient and caregiver of the signs and symptoms of hypersensitivity reactions and IARs and to seek medical care should signs and symptoms occur [see Warnings and Precautions (5.1, 5.2)].

Embryo-Fetal Toxicity

LAMZEDE may cause embryo-fetal harm. Advise the pregnant female of the potential risk to the fetus. Advise a female patient and caregiver to inform their healthcare provider of a known or suspected pregnancy [see Warnings and Precautions (5.3) and Use in Specific Populations (8.1)].

Advise a female of reproductive potential to use effective contraception during treatment and for 14 days after the last dose if LAMZEDE is discontinued [see Use in Specific Populations (8.1, 8.3)].

Manufactured by:
Chiesi Farmaceutici S.p.A.
Via Palermo 26/A, 43122 Parma, Italy
U.S. License No. 2245

Manufactured at:
Patheon Italia S.p.A.,
Ferentino FR, Italy, 03013

Manufactured for:
Chiesi USA, Inc.,
Cary NC, 27518, USA.
Product of Germany.

LAMZEDE is a registered trademark of Chiesi Farmaceutici S.p.A.

CTVA-001-0222-00-SPL

PRINCIPAL DISPLAY PANEL

Principle Display Panel – 1 Vial Carton

NDC 10122-180-02

Rx only

Lamzede®

Velmanase alfa-tycv

for injection

10 mg per vial

For Intravenous infusion after Reconstitution

1 x 10mg Single-dose Vial

Discard unused portion.